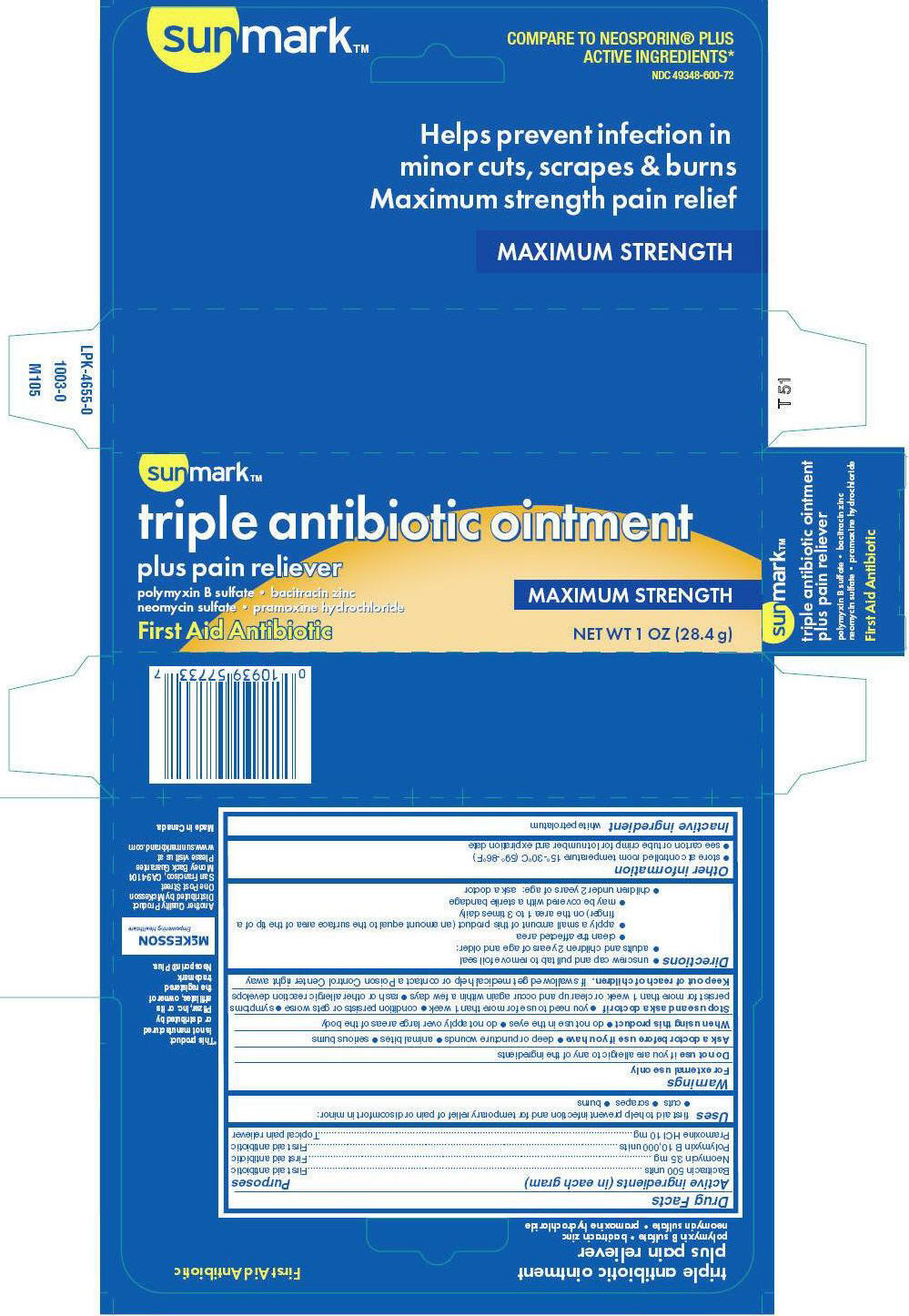 DRUG LABEL: sunmark

NDC: 49348-600 | Form: OINTMENT
Manufacturer: Strategic Sourcing Services LLC
Category: otc | Type: HUMAN OTC DRUG LABEL
Date: 20250715

ACTIVE INGREDIENTS: BACITRACIN ZINC 500 [iU]/1 g; NEOMYCIN SULFATE 3.5 mg/1 g; POLYMYXIN B SULFATE 10000 [iU]/1 g; PRAMOXINE HYDROCHLORIDE 10 mg/1 g
INACTIVE INGREDIENTS: PETROLATUM

sunmark™
triple antibiotic plus pain relief

Drug Facts

ACTIVE INGREDIENT

PURPOSE

Active ingredients (in each gram) | Purposes
Bacitracin 500 units | First aid antibiotic
Neomycin 3.5 mg | First aid antibiotic
Polymyxin B 10,000 units | First aid antibiotic
Pramoxine HCl 10 mg | Topical pain reliever

Uses

first aid to help prevent infection and for temporary relief of pain or discomfort in minor:

- cuts
- scrapes
- burns

Warnings

For external use only

DO NOT USE

Do not useif you are allergic to any of the ingredients

Ask a doctor before use if you have

- deep or puncture wounds
- animal bites
- serious burns

When using this product

- do not use in the eyes
- do not apply over large areas of the body

Stop use and ask a doctor if

- you need to use for more than 1 week
- condition persists or gets worse
- symptoms persist for more than 1 week or clear up and occur again within a few days
- rash or other allergic reaction develops

Keep out of reach of children.If swallowed get medical help or contact a Poison Control Center right away

Directions

- unscrew cap and pull tab to remove foil seal
- adults and children 2 years of age and older:
  - clean the affected area
  - apply a small amount of this product (an amount equal to the surface area of the tip of a finger) on the area 1 to 3 times daily
  - may be covered with a sterile bandage
- children under 2 years of age: ask a doctor

Other information

- store at controlled room temperature 15°-30°C (59°-86°F)
- see carton or tube crimp for lot number and expiration date

Inactive ingredient

white petrolatum

Distributed by McKesson
One Post Street
San Francisco, CA 94104

PRINCIPAL DISPLAY PANEL - 28.4 g Tube Carton

sunmark™

triple antibiotic ointment

plus pain reliever

polymyxin B sulfate • bacitracin zinc
neomycin sulfate • pramoxine hydrochloride

First Aid Antibiotic

MAXIMUM STRENGTH

NET WT 1 OZ (28.4 g)